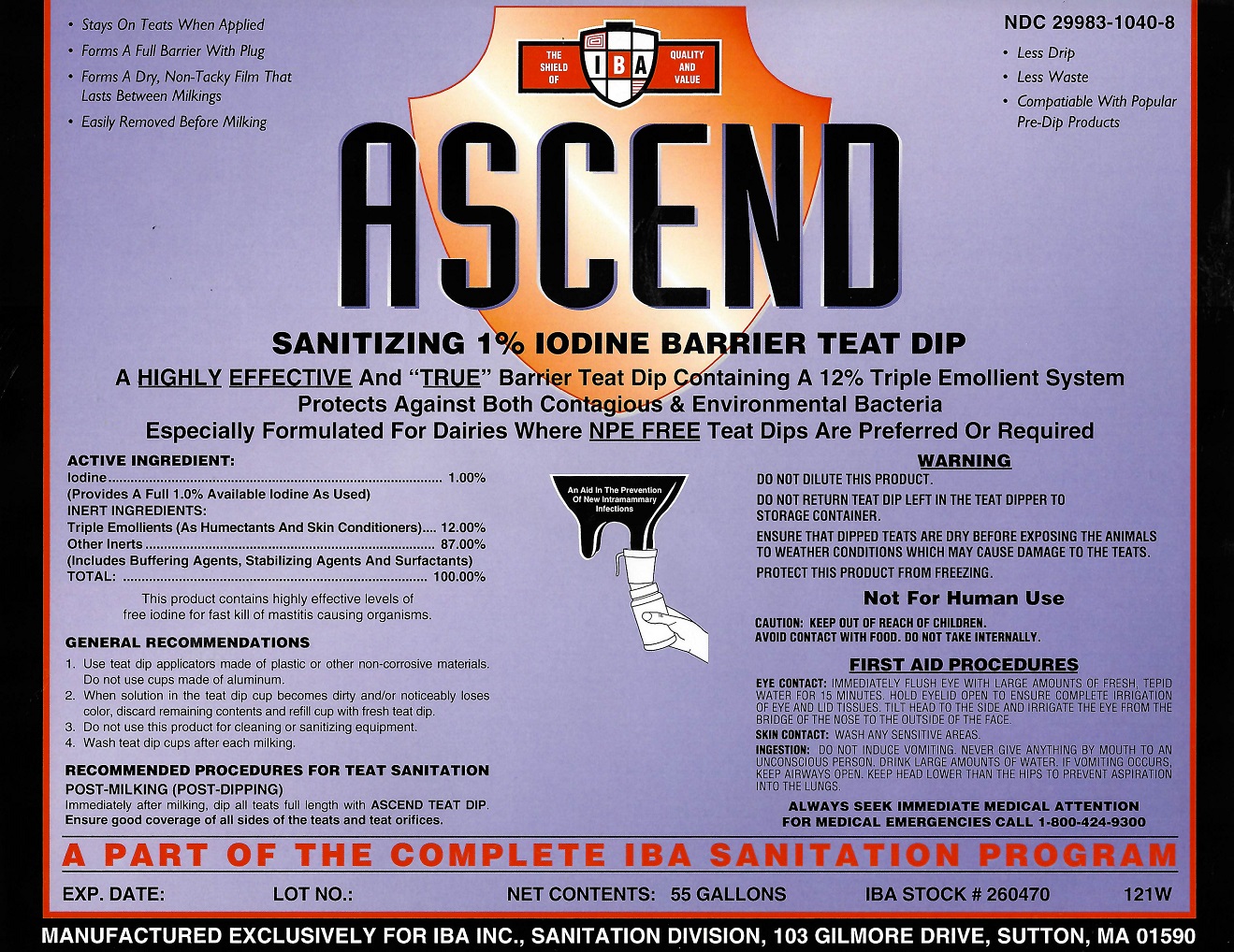 DRUG LABEL: ASCEND
NDC: 29983-1040 | Form: LIQUID
Manufacturer: IBA
Category: animal | Type: OTC ANIMAL DRUG LABEL
Date: 20251126

ACTIVE INGREDIENTS: IODINE 1 kg/1 kg

Ascend

ACTIVE INGREDIENT

Iodine........1%

Inert Ingredients

Triple Emollients...........12.00%

Other Inerts.................87.00%

Total............................100.00%

INDICATIONS AND USAGE

GENERAL RECOMMENDATIONS

1. Use teat dip applicators made of plastic or other non-corrosive materials. Do not use cups made of aluminum.
2. When solution in the teat dip cup becomes dirty and/or noticeably loses color, discard remaining contents and refill cup with fresh teat dip.
3. Do not use this product for cleaning or sanitizing equipment
4. Wash Teat Dip cups after each milking.
RECOMMENDED PROCEDURES FOR TEAT SANITATION
POST-MILKING (POST-DIPPING)
Immediately after milking dip all teats full length with ASCEND Teat Dip. Ensure good coverage of all sides of the teats and teat orifices.

A PART OF THE COMPLETE IBA SANITATION PROGRAM

WARNING

DO NOT DILUTE THIS PRODUCT
DO NOT RETURN TEAT DIP LEFT IN THE TEAT DIPPER TO STORAGE CONTAINER
ENSURE THAT DIPPED TEATS ARE DRY BEFORE EXPOSING THE ANIMALS TO WEATHER CONDITIONS WHICH MAY CAUSE DAMAGE TO THE TEATS.
PROTECT THIS PRODUCT FROM FREEZING.
CAUTION: KEEP OUT OF REACH OF CHILDREN.
AVOID CONTACT WITH FOOD. DO NOT TAKE INTERNALLY.